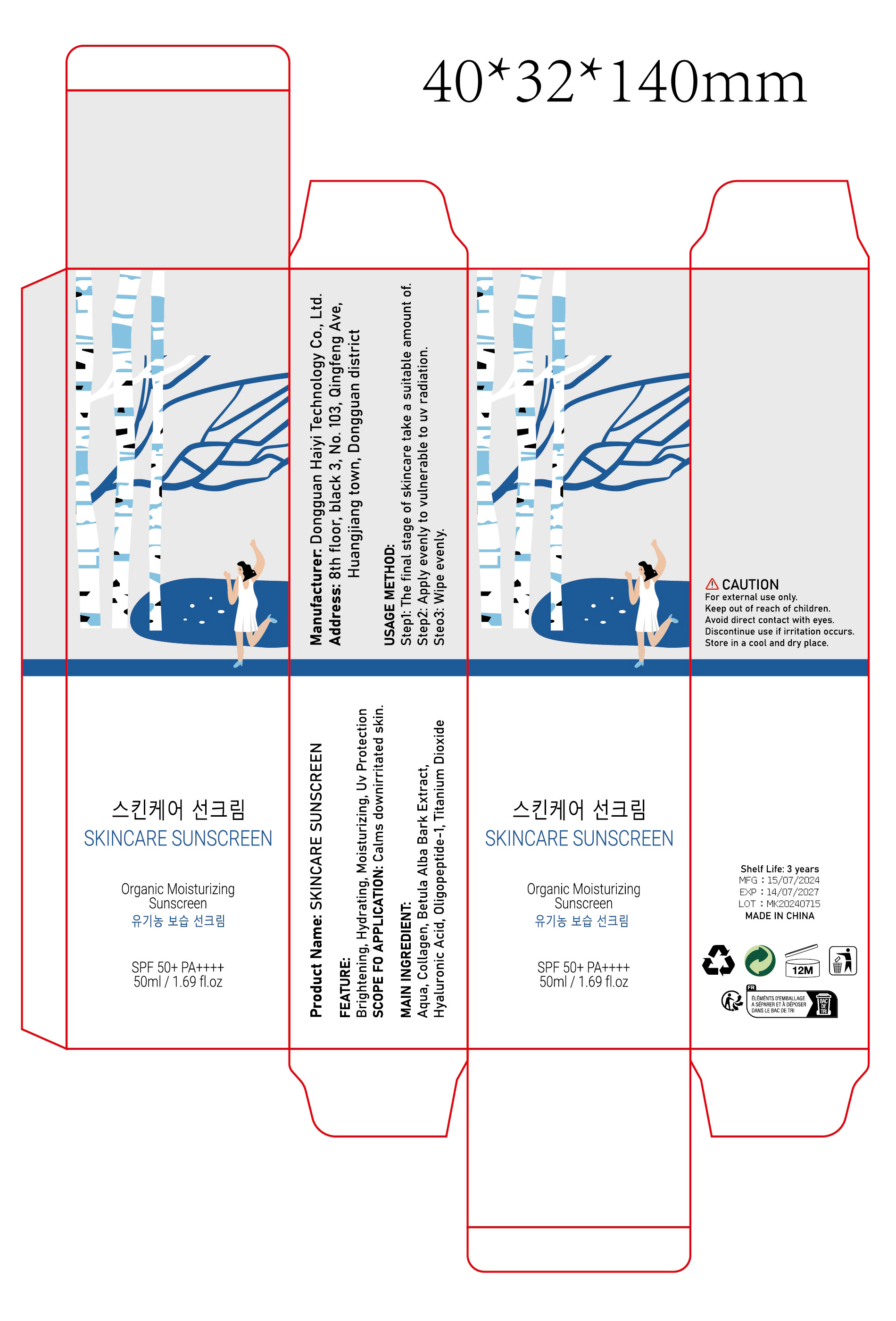 DRUG LABEL: SKINCARE SUNSCREEN
NDC: 84732-010 | Form: CREAM
Manufacturer: Dongguan Haiyi Technology Co.,Ltd.
Category: otc | Type: HUMAN OTC DRUG LABEL
Date: 20240924

ACTIVE INGREDIENTS: WATER 1 mg/50 mL
INACTIVE INGREDIENTS: COLLAGEN ALPHA-1(I) CHAIN BOVINE; OLIGOPEPTIDE-10; TITANIUM DIOXIDE; BETULA PUBESCENS BARK; HYALURONIC ACID

Active ingredient

Aqua

Inactive ingredient

Collagen,Betula Alba Bark Extract,
Hyaluronic Acid,Oligopeptide-1,Titanium Dioxide

Purpose section

Brightening,Hydrating,Moisturizing,Uv Protection

Warning

For external use only.

Keep out of reach of children.
Avoid direct contact with eyes.
Discontinue use if irritation occurs.
Store in a cool and dry place.

stop use

This product may cause allergic reactions in asmall number of people.
lf you experience any discomfort,please stop using it immediately.

not use

Not suitable for use by children, pregnantor breastfeeding people.

OUT OF CHILDREN

KEEP THE PRODUCT OUT OF REACH OF CHILDREN to

HOW TO USE

Step1: The final stage of skincare take a suitable amount of.
Step2: Apply evenly to vulnerable to uv radiation.
Step3: Wipe evenly.

Dosage

Once a day when the sun comes out